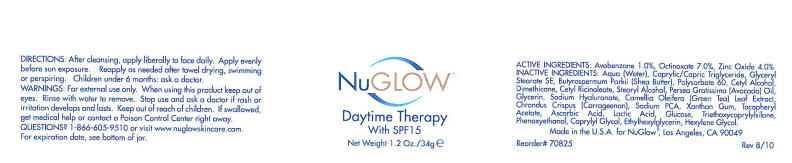 DRUG LABEL: NuGLOW 
NDC: 65113-8503 | Form: CREAM
Manufacturer: G.S. COSMECEUTICAL USA, INC.
Category: otc | Type: HUMAN OTC DRUG LABEL
Date: 20110208

ACTIVE INGREDIENTS: AVOBENZONE 1 g/100 g; OCTINOXATE 7 g/100 g; ZINC OXIDE 4 g/100 g
INACTIVE INGREDIENTS: WATER; CETYL ALCOHOL; DIMETHICONE; STEARYL ALCOHOL; AVOCADO OIL; GLYCERIN; CAMELLIA OLEIFERA LEAF; XANTHAN GUM; ASCORBIC ACID; LACTIC ACID; TRIETHOXYCAPRYLYLSILANE; PHENOXYETHANOL; CAPRYLYL GLYCOL; HEXYLENE GLYCOL

NuGLOW®

DIRECTIONS

After cleansing, apply liberally to face daily. Apply evenly before sun exposure. Reapply as needed after towel drying, swimming or perspiring.

Children under 6 months: ask a doctor.

WARNINGS

For external use only.

When using this product keep out of eyes. Rinse with water to remove.

Stop use and ask a doctor if rash or irritation develops and lasts.

Keep out of reach of children. If swallowed, get medical help or contact a Poison Control Center right away.

QUESTIONS?

1-866-605-9510 or visit www.nuglowskincare.com.

PURPOSE

Daytime Therapy With SPF15

ACTIVE INGREDIENTS

Avobenzone 1.0%, Octinoxate 7.0%, Zinc Oxide 4.0%.

INACTIVE INGREDIENTS

Aqua (Water), Caprylic/Capric Triglyceride, Glyceryl Stearate SE, Butyrospermum Parkii (Shea Butter), Polysorbate 60, Cetyl Alcohol, Dimethicone, Cetyl Ricinoleate, Stearyl Alcohol, Persea Gratissima (Avocado) Oil, Glycerin, Sodium Hyaluronate, Camellia Oleifera (Green Tea) Leaf Extract, Chrondrus Crispus (Carrageenan), Sodium PCA, Xanthan Gum, Tocopheryl Acetate, Ascorbic Acid, Lactic Acid, Glucose, Triethoxycaprylylsilane, Phenoxyethanol, Caprylyl Glycol, Ethylhexylglycerin, Hexylene Glycol.

For expiration date, see bottom of jar.

Made in the U.S.A. for NuGlow, Los Angeles, CA 90049

Reorder# 70825
Rev 8/10

PRINCIPAL DISPLAY PANEL - 34g Jar Label

NuGlow®

Daytime Therapy
With SPF15

Net Weight 1.2 Oz./34g e